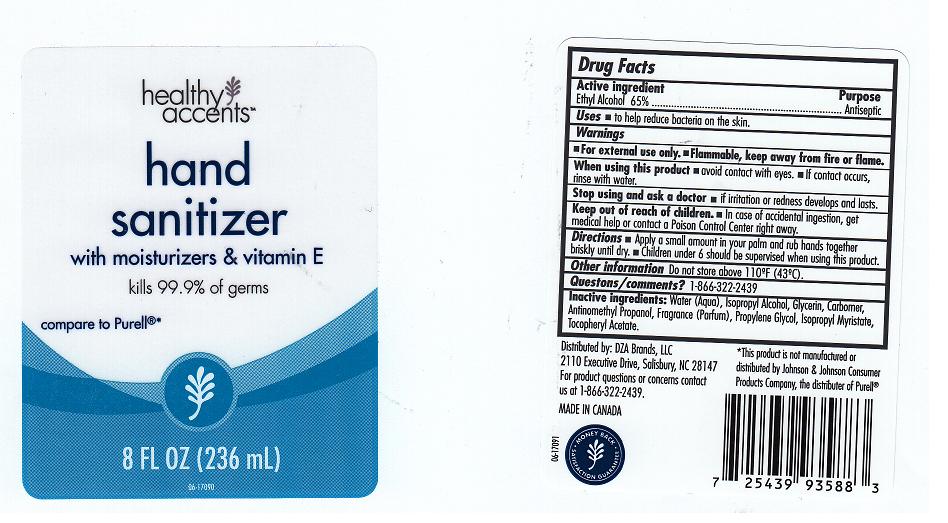 DRUG LABEL: HAND SANITIZER
NDC: 55316-267 | Form: GEL
Manufacturer: DZA BRANDS
Category: otc | Type: HUMAN OTC DRUG LABEL
Date: 20111012

ACTIVE INGREDIENTS: ALCOHOL 65 mL/100 mL
INACTIVE INGREDIENTS: WATER; ISOPROPYL ALCOHOL; GLYCERIN; CARBOMER 934; AMINOMETHYLPROPANOL; PROPYLENE GLYCOL; ISOPROPYL MYRISTATE; .ALPHA.-TOCOPHEROL ACETATE, D-

DRUG FACTS

ACTIVE INGREDIENT

ETHYL ALCOHOL 65 PERCENT

PURPOSE

ANTISEPTIC

USES

TO HELP REDUCE BACTERIA ON THE SKIN.

WARNINGS

FOR EXTERNAL USE ONLY. FLAMMABLE, KEEP AWAY FROM FIRE OR FLAME.

WHEN USING THIS PRODUCT

- AVOID CONTACT WITH EYES.

- IF CONTACT OCCURS, RINSE WITH WATER.

STOP USING THIS PRODUCT AND ASK DOCTOR IF

IRRITATION OR REDNESS DEVELOPS AND LASTS.

KEEP OUT OF REACH OF CHILDREN

IN CASE OF ACCIDENTAL INGESTION, GET MEDICAL HELP OR CONTACT A POISON CONTROL CENTER RIGHT AWAY.

DIRECTIONS

APPLY A SMALL AMOUNT IN YOUR PALM AND RUB HANDS TOGETHER BRISKLY UNTIL DRY. CHILDREN UNDER 6, SHOULD BE SUPERVISED WHEN USING THIS PRODUCT.

OTHER INFORMATION

DO NOT STORE ABOVE 110^0F (43^0C).

QUESTIONS OR COMMENTS

1-866-322-2439

INACTIVE INGREDIENTS

WATER, ISOPROPYL ALCOHOL, GLYCERIN, CARBOMER, AMINOMETHYL PROPANOL, FRAGRANCE, PROPYLENE GLYCOL, ISOPROPYL MYRISTATE, TOCOPHERYL ACETATE.